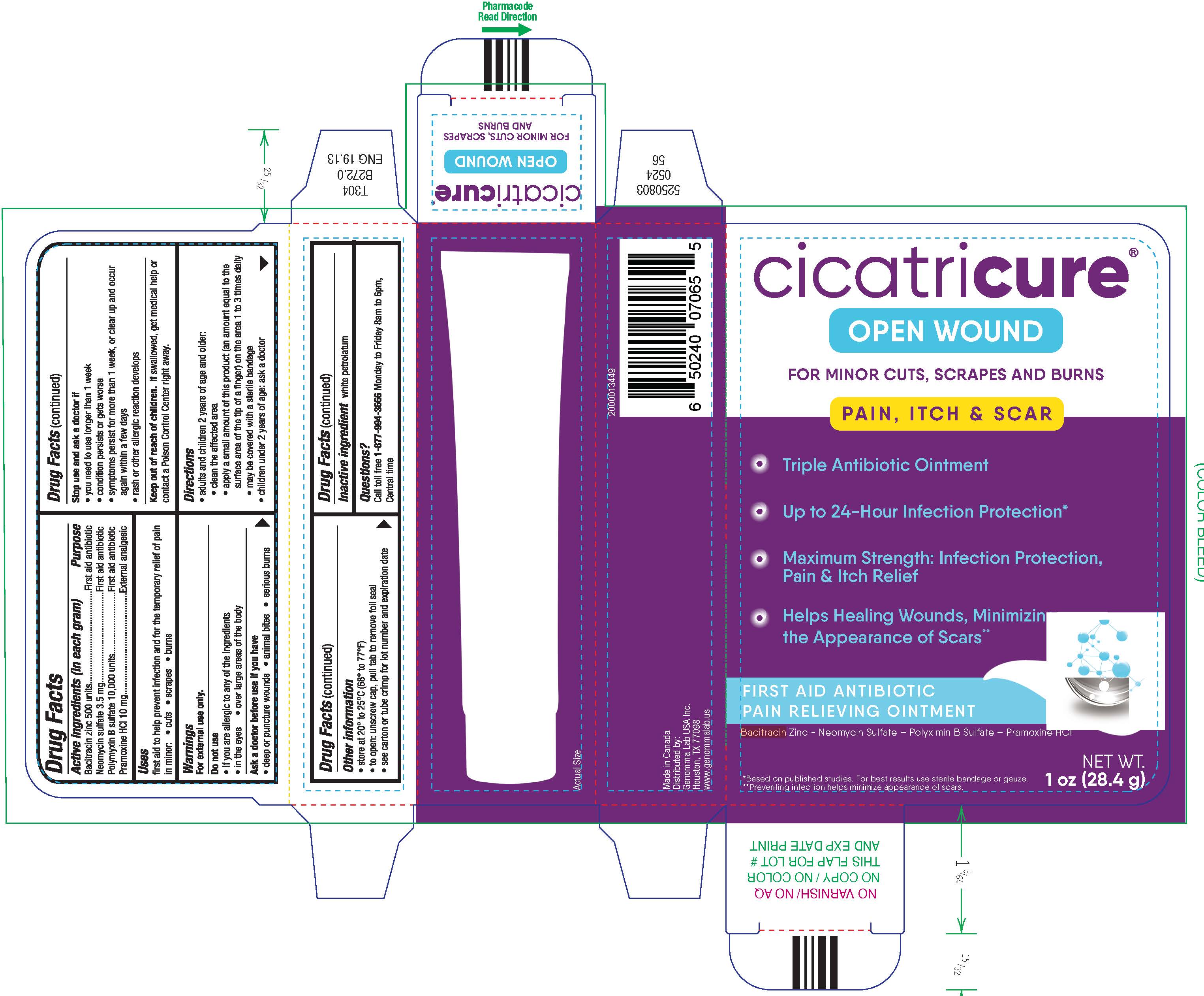 DRUG LABEL: TRIPLE ANTIBIOTIC PLUS PAIN RELIEF
NDC: 50066-202 | Form: OINTMENT
Manufacturer: GENOMMA LAB USA, INC.
Category: otc | Type: HUMAN OTC DRUG LABEL
Date: 20250702

ACTIVE INGREDIENTS: BACITRACIN ZINC 500 [USP'U]/1 g; NEOMYCIN SULFATE 3.5 mg/1 g; POLYMYXIN B SULFATE 10000 [USP'U]/1 g; PRAMOXINE HYDROCHLORIDE 10 mg/1 g
INACTIVE INGREDIENTS: PETROLATUM

TRIPLE ANTIBIOTIC PLUS PAIN RELIEF

Drug Facts

ACTIVE INGREDIENT

Active ingredients (in each gram) | Purpose
Bacitracin zinc 500 units | First aid antibiotic
Neomycin sulfate 3.5 mg | First aid antibiotic
Polymyxin B sulfate 10,000 units | First aid antibiotic
Pramoxine HCl 10 mg | External analgesic

Uses

first aid to help prevent infection and for the temporary relief of pain in minor:

- cuts
- scrapes
- burns

Warnings

For external use only.

Do not use

- if you are allergic to any of the ingredients
- in the eyes
- over large areas of the body

Ask a doctor before use if you have

- deep or puncture wounds
- animal bites
- serious burns

Stop use and ask a doctor if

- you need to use longer than 1 week
- condition persists or gets worse
- symptoms persist for more than 1 week, or clear up and occur again within a few days
- rash or other allergic reaction develops

Keep out of reach of children.If swallowed, get medical help or contact a Poison Control Center right away.

Directions

- adults and children 2 years of age and older:
  - clean the affected area
  - apply a small amount of this product (an amount equal to the surface area of the tip of a finger) on the area 1 to 3 times daily
  - may be covered with a sterile bandage
- children under 2 years of age: ask a doctor

Other information

- store at 20° to 25°C (68° to 77°F)
- to open: unscrew cap, pull tab to remove foil seal
- see carton or tube crimp for lot number and expiration date

Inactive ingredient

white petrolatum

Questions?

Call toll free 1-877-994-3666Monday to Friday 8am to 6pm, Central time

Distributed by:
Genomma Lab USA Inc.
Houston, TX 77098

PRINCIPAL DISPLAY PANEL - 28.4 g Tube Carton

cicatricure®

OPEN WOUND

FOR MINOR CUTS, SCRAPES AND BURNS

PAIN, ITCH & SCAR

- Triple Antibiotic Ointment
- Up to 24-Hour Infection Protection
- Maximum Strength: Infection Protection,
  Pain & Itch Relief
- Helps Healing Wounds, Minimizing
  the Appearance of Scars**

FIRST AID ANTIBIOTIC
PAIN RELIEVING OINTMENT

Bacitracin Zinc – Neomycin Sulfate – Polyximin B Sulfate – Pramoxine HCl

*Based on published studies. For best results use sterile bandage or gauze.
**Preventing infection helps minimize appearance of scars.

NET WT.
1 oz (28.4 g)